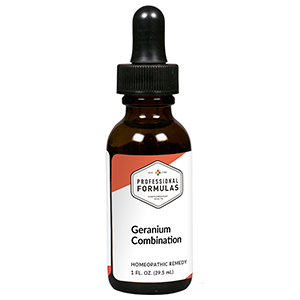 DRUG LABEL: Geranium Combination
NDC: 63083-9224 | Form: LIQUID
Manufacturer: Professional Complementary Health Formulas
Category: homeopathic | Type: HUMAN OTC DRUG LABEL
Date: 20190815

ACTIVE INGREDIENTS: GERANIUM ROBERTIANUM WHOLE 2 [hp_X]/29.5 mL; ALOE 4 [hp_X]/29.5 mL; COLCHICUM AUTUMNALE BULB 4 [hp_X]/29.5 mL; VERATRUM ALBUM ROOT 4 [hp_X]/29.5 mL; SILVER NITRATE 6 [hp_X]/29.5 mL; ARSENIC TRIOXIDE 6 [hp_X]/29.5 mL; CITRULLUS COLOCYNTHIS FRUIT PULP 6 [hp_X]/29.5 mL; PODOPHYLLUM 6 [hp_X]/29.5 mL; FERROSOFERRIC PHOSPHATE 10 [hp_X]/29.5 mL; ANTIMONY TRISULFIDE 12 [hp_X]/29.5 mL; MERCURIC CHLORIDE 12 [hp_X]/29.5 mL
INACTIVE INGREDIENTS: ALCOHOL; WATER

R224

ACTIVE INGREDIENTS

Geranium robertianum 2X
Aloe socotrina 4X
Colchicum autumnale 4X
Veratrum album 4X
Argentum nitricum 6X
Arsenicum album 6X
Colocynthis 6X
Podophyllum peltatum 6X
Ferrum phosphoricum 10X
Antimonium crudum 12X
Mercurius corrosivus 12X

QUESTIONS

Professional Formulas

PO Box 2034 Lake Oswego, OR 97035

INDICATIONS

For the temporary relief of diarrhea, indigestion, stomach cramping, or nausea.*

PURPOSE

*Claims based on traditional homeopathic practice, not accepted medical evidence. Not FDA evaluated.

WARNINGS

Do not use for more than 30 days. If symptoms do not improve or are accompanied by a fever, consult a doctor. Keep out of the reach of children. In case of overdose, get medical help or contact a poison control center right away. If pregnant or breastfeeding, ask a healthcare professional before use.

Keep out of the reach of children.

PREGNANCY OR BREAST FEEDING

If pregnant or breastfeeding, ask a healthcare professional before use.

DIRECTIONS

Place drops under tongue 30 minutes before/after meals. Adults and children 12 years and over: Take 10 drops up to 3 times per day. Consult a physician for use in children under 12 years of age.

OTHER INFORMATION

Tamper resistant. If seal is broken, do not use. After opening, close container tightly and store at room temperature away from heat.

INACTIVE INGREDIENTS

40% ethanol, purified water.

LABEL

Est 1985

Professional Formulas

Complementary Health

Geranium Combination

Homeopathic Remedy

1 FL. OZ. (29.5 mL)